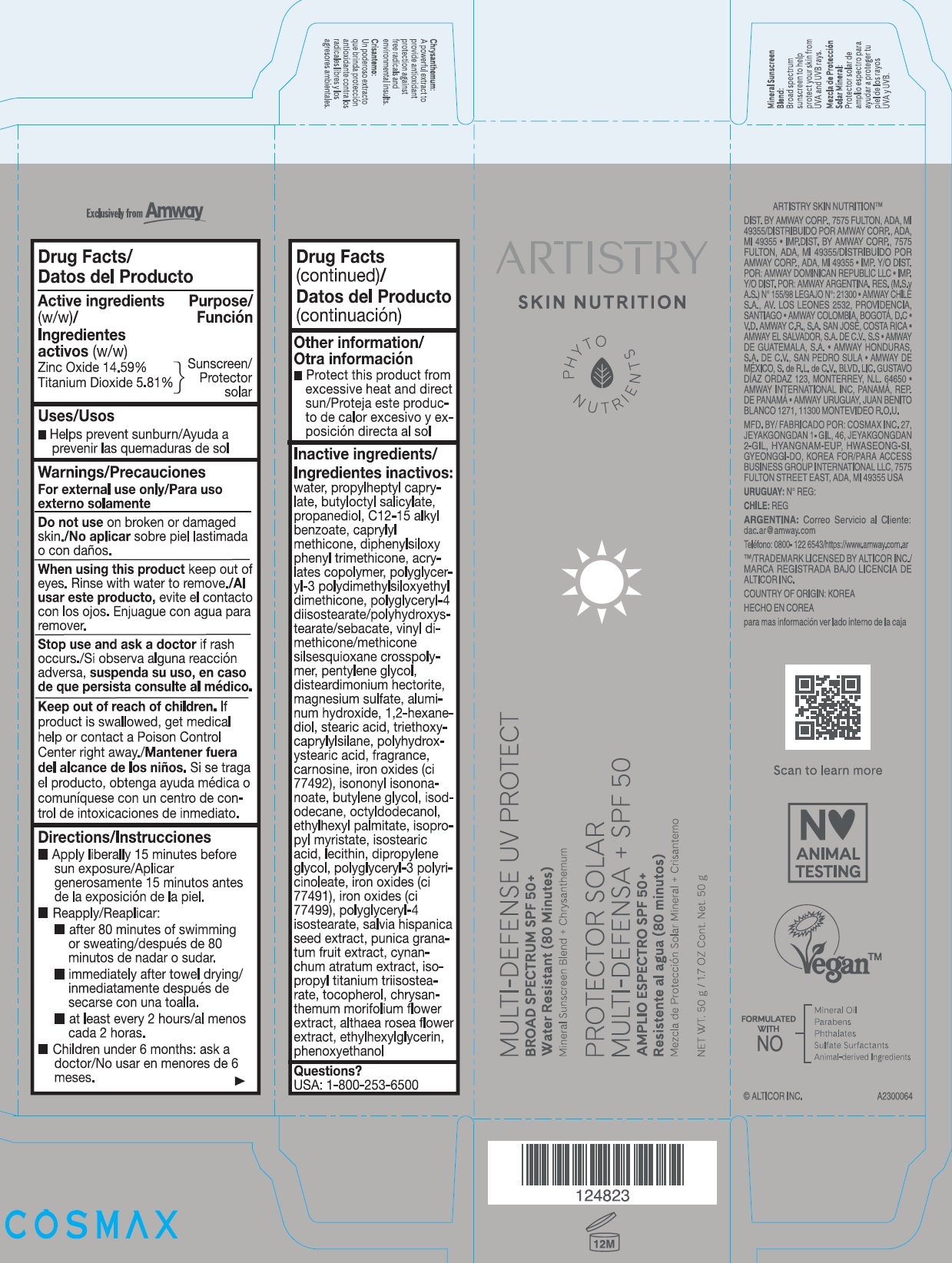 DRUG LABEL: Artistry Skin Nutrition Multi-Defense UV Protect
NDC: 10056-531 | Form: LOTION
Manufacturer: Access Business Group LLC
Category: otc | Type: HUMAN OTC DRUG LABEL
Date: 20231023

ACTIVE INGREDIENTS: ZINC OXIDE 145.9 mg/1 g; TITANIUM DIOXIDE 58.1 mg/1 g
INACTIVE INGREDIENTS: WATER; PROPYLHEPTYL CAPRYLATE; BUTYLOCTYL SALICYLATE; PROPANEDIOL; ALKYL (C12-15) BENZOATE; CAPRYLYL TRISILOXANE; DIPHENYLSILOXY PHENYL TRIMETHICONE; POLYGLYCERYL-4 DIISOSTEARATE/POLYHYDROXYSTEARATE/SEBACATE; VINYL DIMETHICONE/METHICONE SILSESQUIOXANE CROSSPOLYMER; PENTYLENE GLYCOL; DISTEARDIMONIUM HECTORITE; MAGNESIUM SULFATE, UNSPECIFIED FORM; ALUMINUM HYDROXIDE; 1,2-HEXANEDIOL; STEARIC ACID; TRIETHOXYCAPRYLYLSILANE; CARNOSINE; FERRIC OXIDE YELLOW; ISONONYL ISONONANOATE; BUTYLENE GLYCOL; ISODODECANE; OCTYLDODECANOL; ETHYLHEXYL PALMITATE; ISOPROPYL MYRISTATE; ISOSTEARIC ACID; DIPROPYLENE GLYCOL; FERRIC OXIDE RED; FERROSOFERRIC OXIDE; POLYGLYCERYL-4 ISOSTEARATE; CHIA SEED; POMEGRANATE; ISOPROPYL TITANIUM TRIISOSTEARATE; TOCOPHEROL; CHRYSANTHEMUM X MORIFOLIUM FLOWER; ALCEA ROSEA FLOWER; ETHYLHEXYLGLYCERIN; PHENOXYETHANOL

Artistry Skin Nutrition™ Multi-Defense UV Protect SPF 50

Active ingredients (w/w)

Zinc Oxide 14.59%

Titanium Dioxide 5.81%

Purpose

Sunscreen

Uses

- Helps prevent sunburn

Warnings

For external use only

Do not use

on broken or damaged skin

When using this product

keep out of eyes. Rinse with water to remove.

Stop use and ask a doctor

if rash occurs

Keep out of reach of children.

If product is swallowed, get medical help or contact a Poison Control Center right away.

Directions

- Apply liberally 15 minutes before sun exposure
- Reapply
- after 80 minutes of swimming or sweating
- immediately after towel drying
- at least every 2 hours
- Children under 6 months: ask a doctor

Other information

- Protect this product from excessive heat and direct sun

Inactive ingredients

water, propylheptyl caprylate, butyloctyl salicylate, propanediol, C12-15 alkyl benzoate, caprylyl methicone, diphenylsiloxy phenyl trimethicone, acrylates copolymer, polyglyceryl-3 polydimethylsiloxyethyl dimethicone, polyglyceryl-4 diisostearate/polyhydroxystearate/sebacate, vinyl dimethicone/methicone silsesquioxane crosspolymer, pentylene glycol, disteardimonium hectorite, magnesium sulfate, aluminum hydroxide, 1,2-hexanediol, stearic acid, triethoxycaprylylsilane, polyhydroxystearic acid, fragrance, carnosine, iron oxides (ci 77492), isononyl isononanoate, butylene glycol, isododecane, octyldodecanol, ethylhexyl palmitate, isopropyl myristate, isostearic acid, lecithin, dipropylene glycol, polyglyceryl-3 polyricinoleate, iron oxides (ci 77491), iron oxides (ci 77499), polyglyceryl-4 isostearate, salvia hispanica seed extract, punica granatum fruit extract, cynanchum atratum extract, isopropyl titanium triisostearate, tocopherol, chrysanthemum morifolium flower extract, althaea rosea flower extract, ethylhexylglycerin, phenoxyethanol

Questions?

USA: 1-800-253-6500